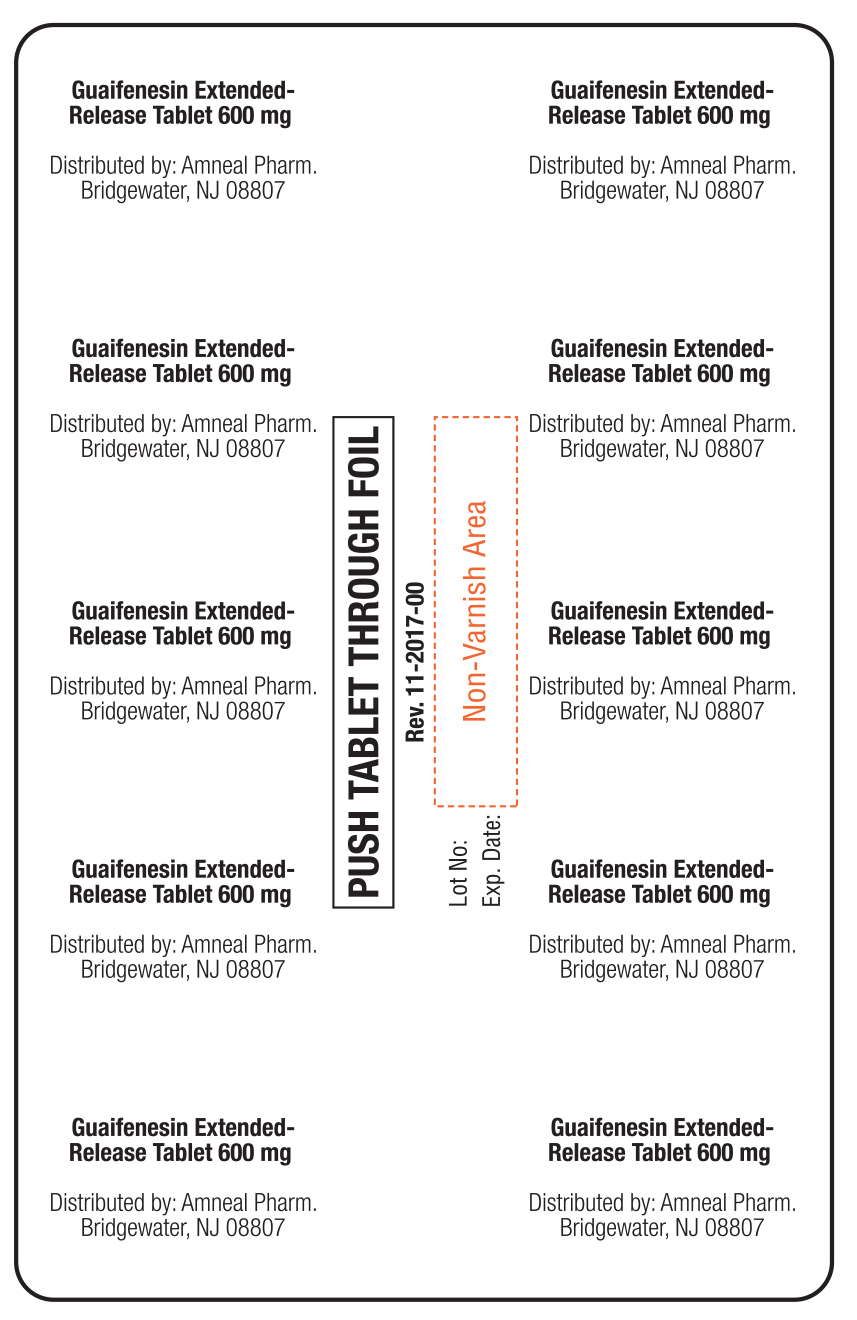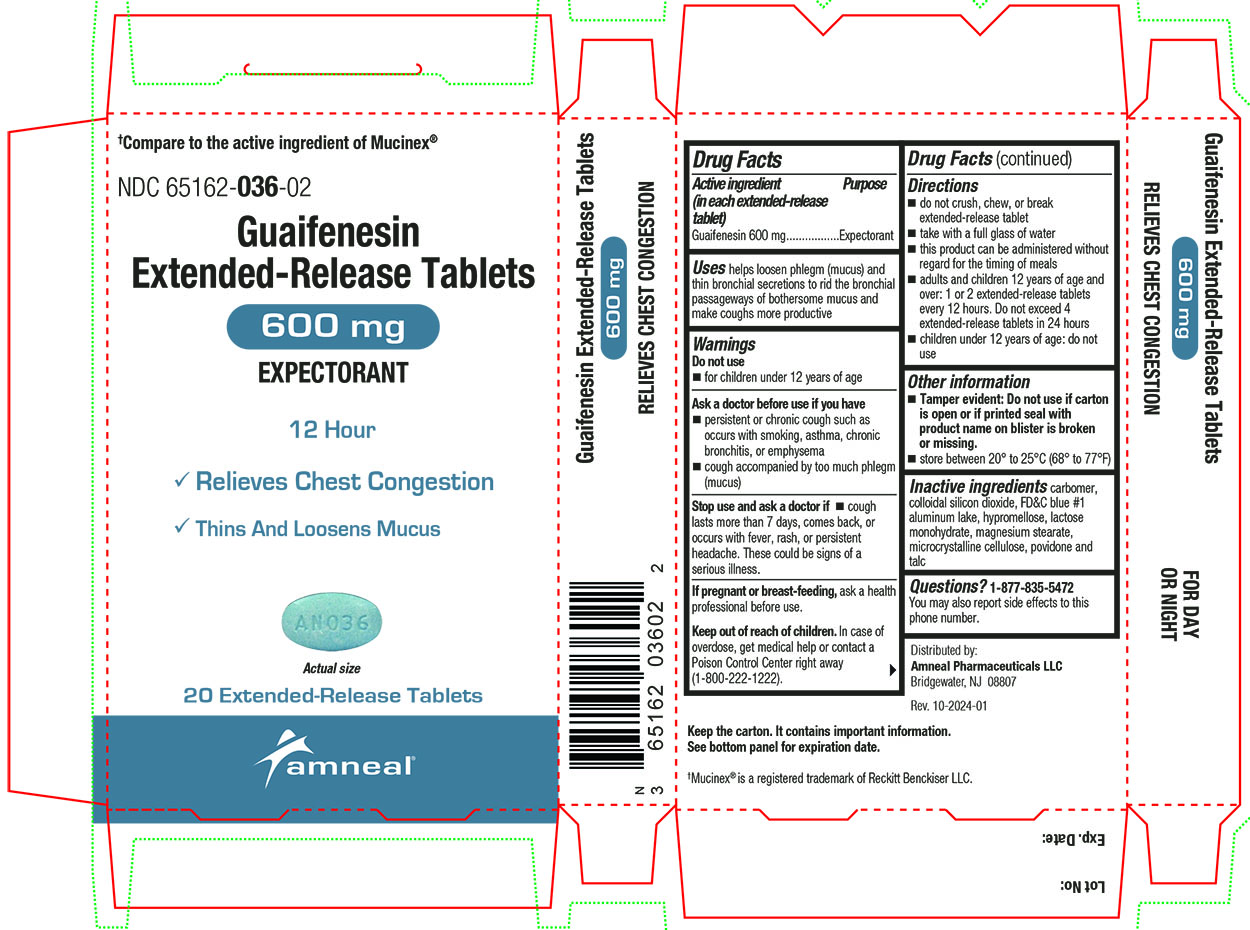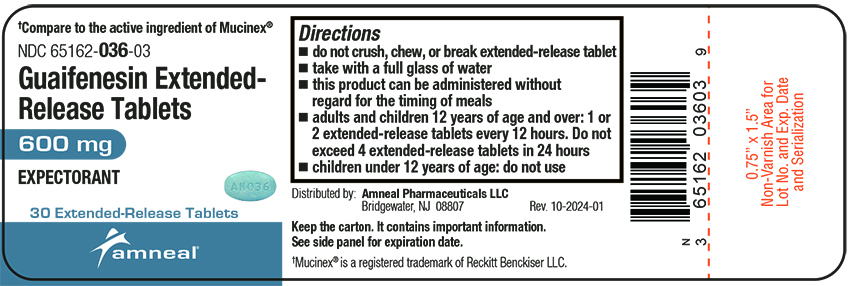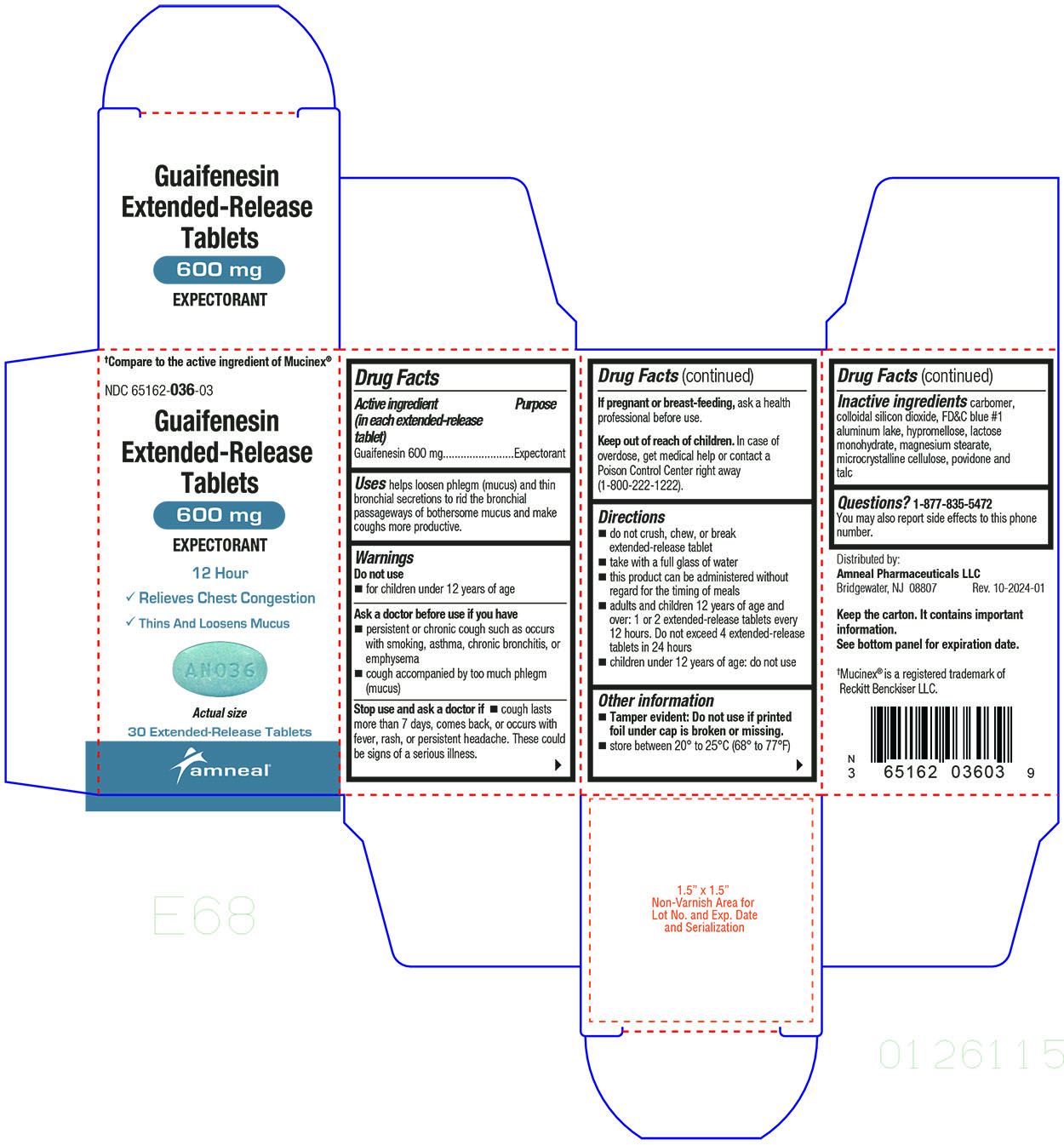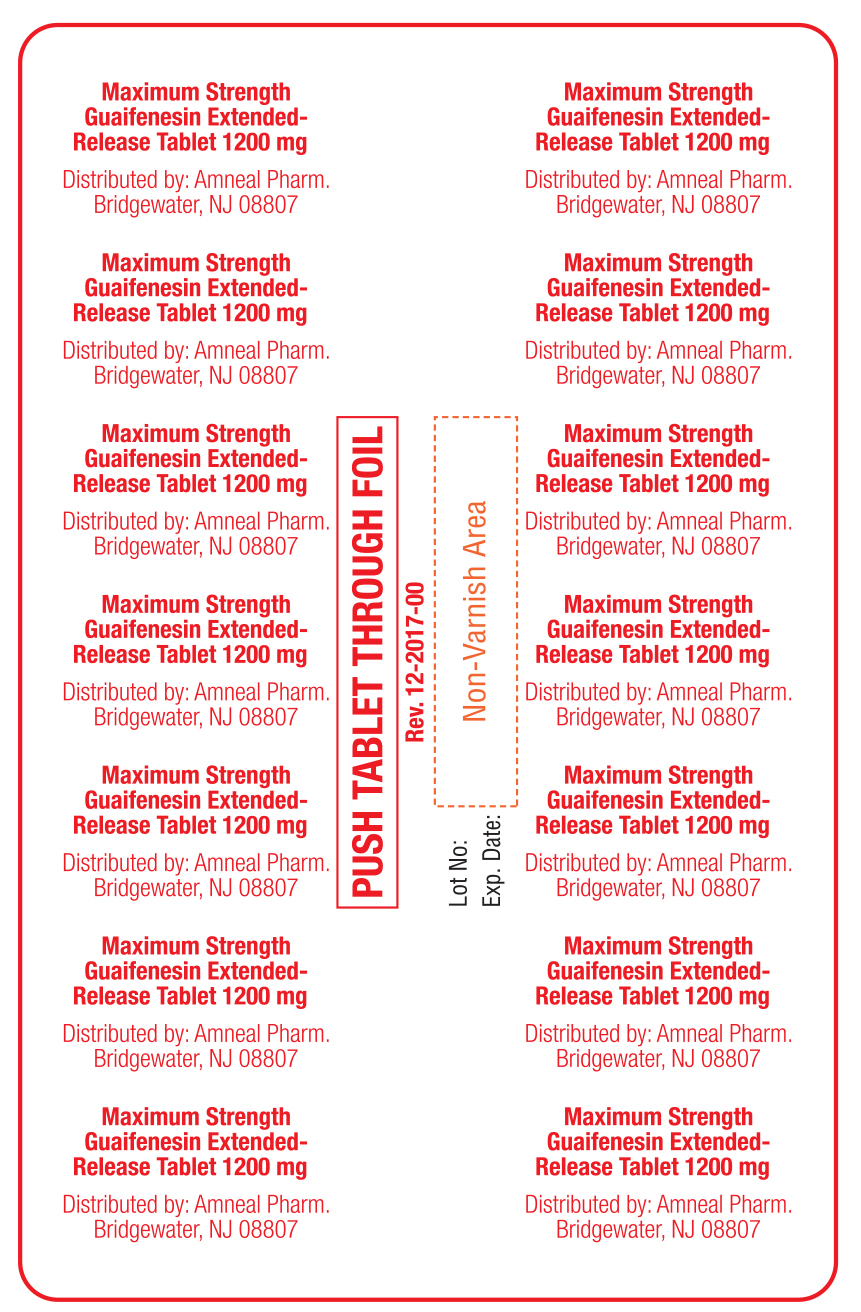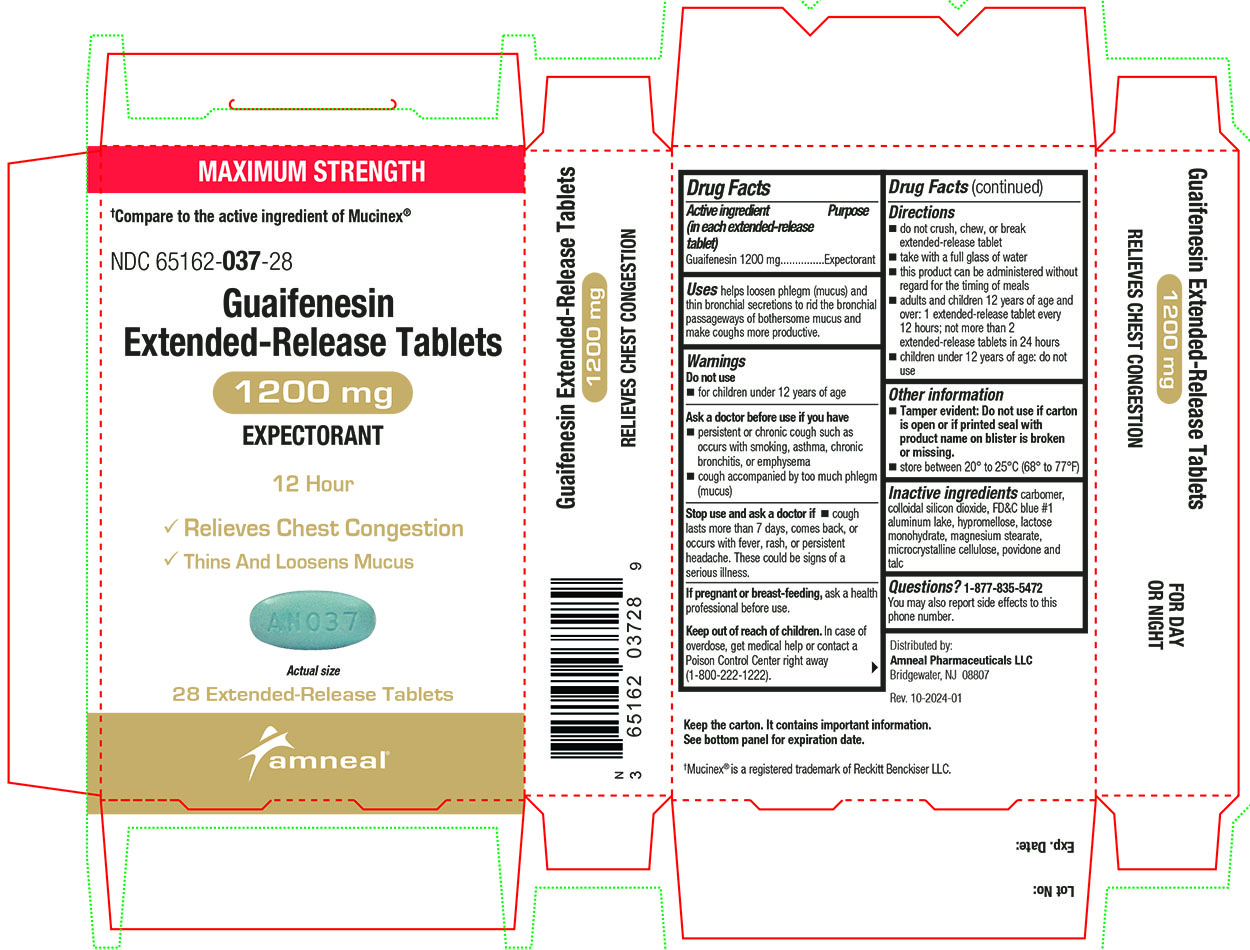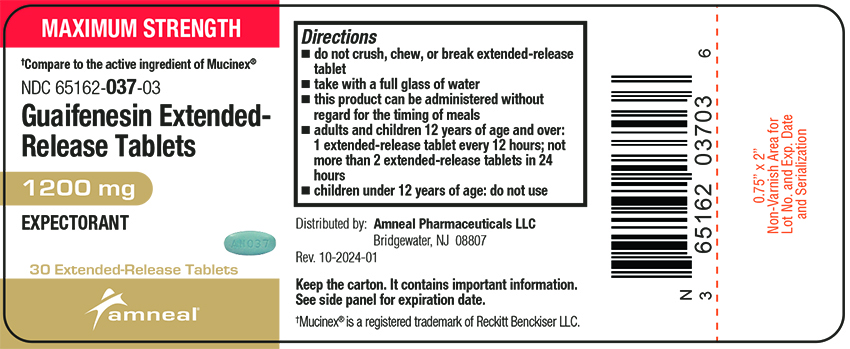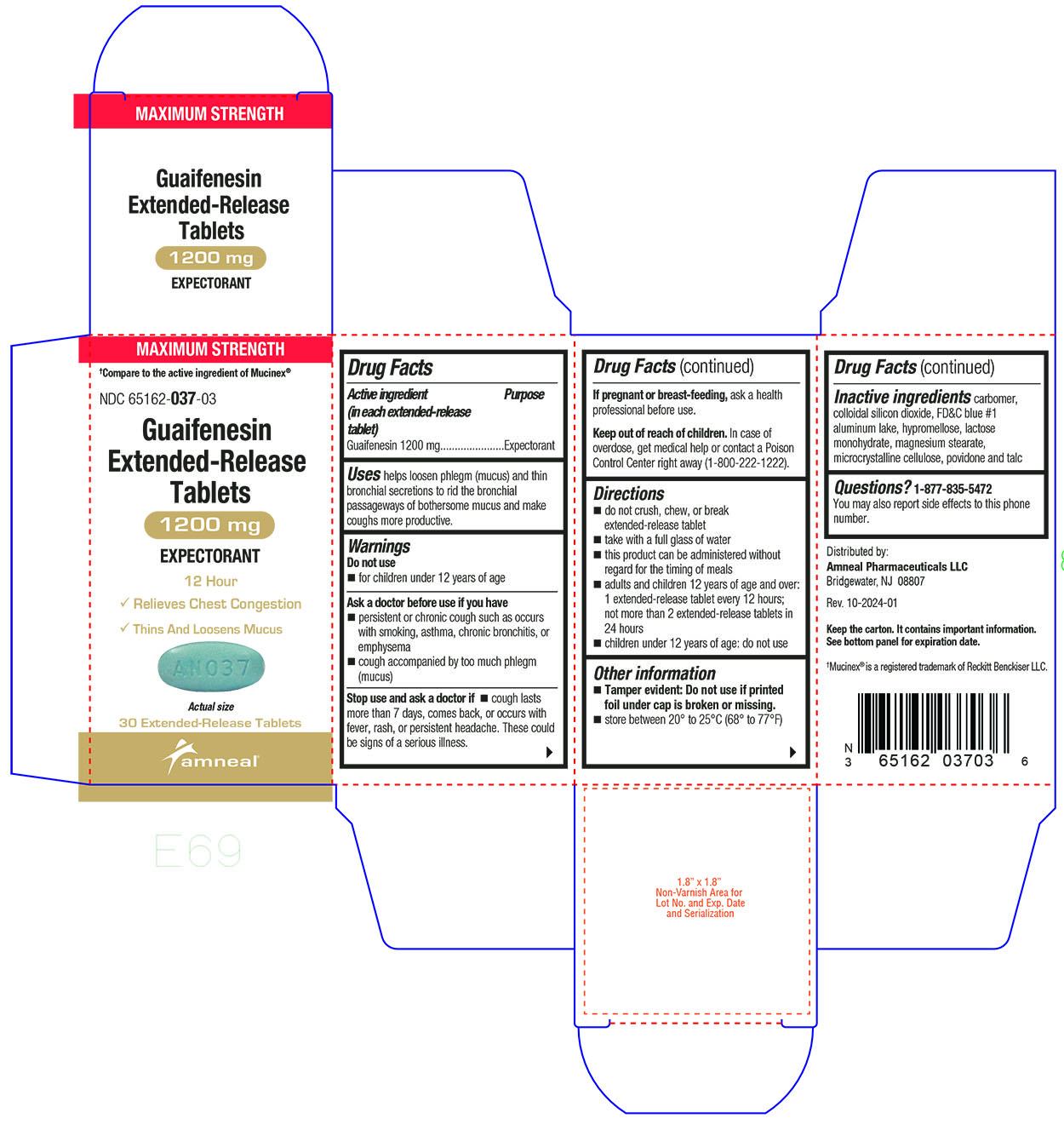 DRUG LABEL: Guaifenesin
NDC: 65162-036 | Form: TABLET, EXTENDED RELEASE
Manufacturer: Amneal Pharmaceuticals LLC
Category: otc | Type: HUMAN OTC DRUG LABEL
Date: 20241007

ACTIVE INGREDIENTS: GUAIFENESIN 600 mg/1 1
INACTIVE INGREDIENTS: CARBOMER COPOLYMER TYPE A; SILICON DIOXIDE; FD&C BLUE NO. 1; HYPROMELLOSES; LACTOSE MONOHYDRATE; MAGNESIUM STEARATE; CELLULOSE, MICROCRYSTALLINE; POVIDONE; TALC

Guaifenesin Extended-Release Tablets

Active ingredient(s)

Active ingredient (in each extended-release tablet)

Guaifenesin 600 mg

Active ingredient (in each extended-release tablet)

Guaifenesin 1200 mg

Purpose

Expectorant

Uses

helps loosen phlegm (mucus) and thin bronchial secretions to rid the bronchial passageways of bothersome mucus and make coughs more productive.

Warnings

Do not use

- for children under 12 years of age

Ask a doctor before use if you have

- persistent or chronic cough such as occurs with smoking, asthma, chronic bronchitis, or emphysema
- cough accompanied by too much phlegm (mucus)

Stop use and ask a doctor if

- cough lasts more than 7 days, comes back, or occurs with fever, rash, or persistent headache. These could be signs of a serious illness.

Pregnancy/Breastfeeding

If pregnant or breast-feeding, ask a health professional before use.

Keep out of reach of children

In case of overdose, get medical help or contact a Poison Control Center right away (1-800-222-1222).

Directions

600 mg

- do not crush, chew, or break extended-release tablet
- take with a full glass of water
- this product can be administered without regard for the timing of meals
- adults and children 12 years of age and over: 1 or 2 extended-release tablets every 12 hours. Do not exceed 4 extended-release tablets in 24 hours.
- children under 12 years of age: do not use

1200 mg

- do not crush, chew, or break extended-release tablet
- take with a full glass of water
- this product can be administered without regard for the timing of meals
- adults and children 12 years of age and over: 1 extended-release tablet every 12 hours; not more than 2 extended-release tablets in 24 hours.
- children under 12 years of age: do not use

Other information

- Tamper evident: Do not use if printed foil under cap is broken or missing.

Storage

- store between 20° to 25°C (68° to 77°F)

Inactive ingredients

carbomer, colloidal silicon dioxide, FD&C blue #1 aluminum lake, hypromellose, lactose monohydrate, magnesium stearate, microcrystalline cellulose, povidone and talc

Questions

1-877-835-5472 You may also report side effects to this phone number.

Distributed by:
Amneal Pharmaceuticals LLC
Bridgewater, NJ 08807

Rev. 10-2024-01